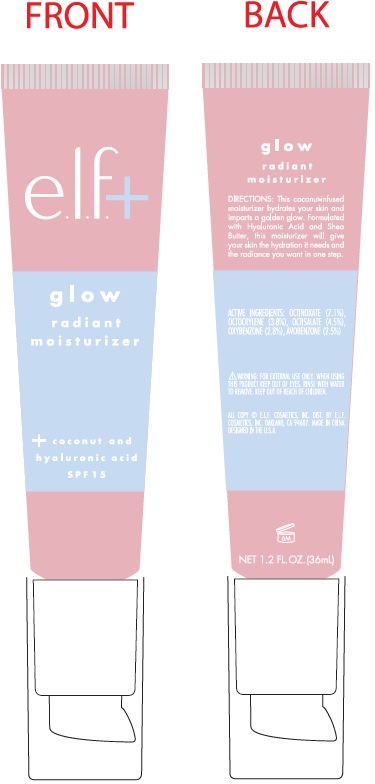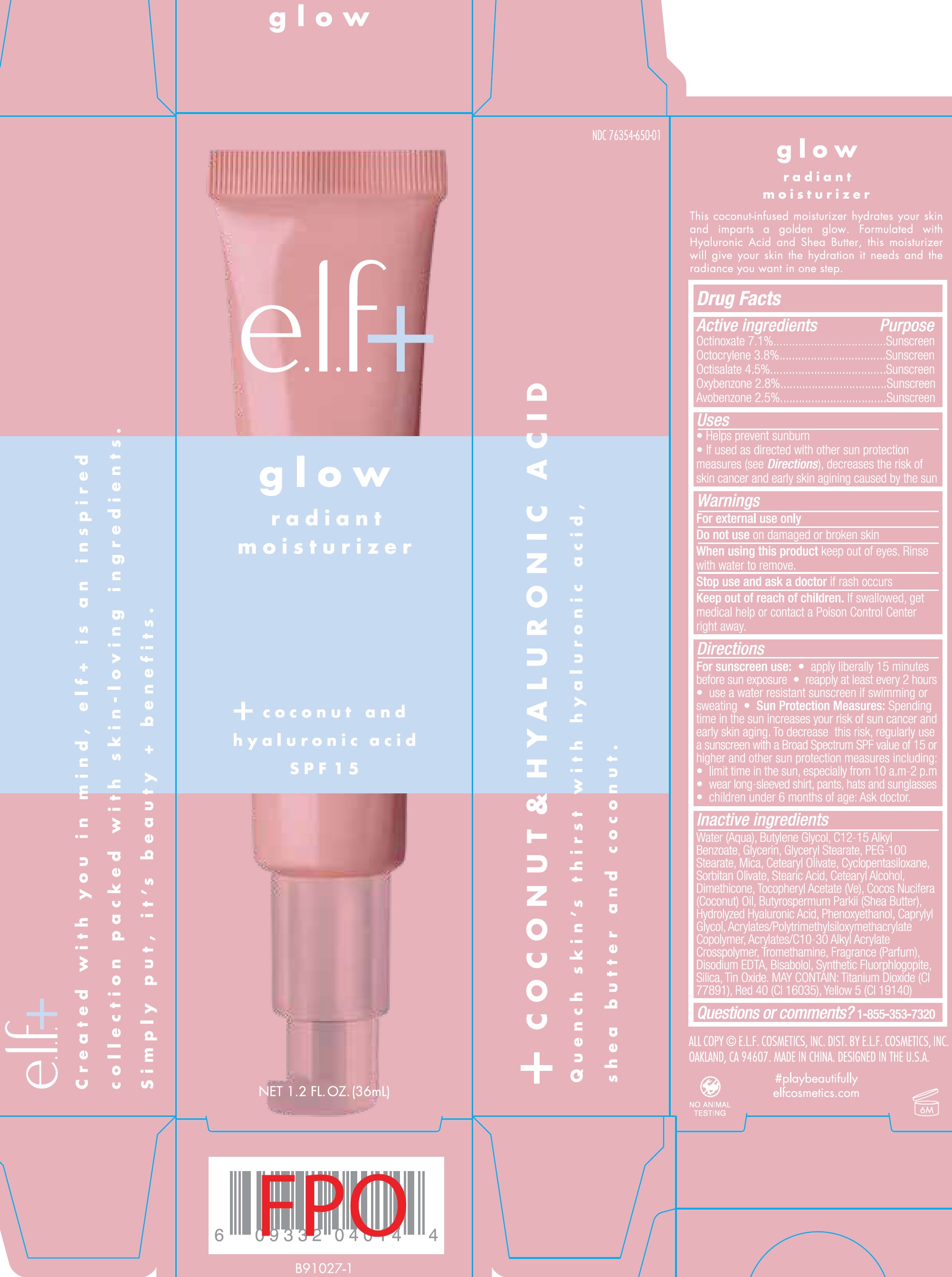 DRUG LABEL: Glow Radiant Moisturizer SPF 15
NDC: 76354-650 | Form: CREAM
Manufacturer: e.l.f. Cosmetics, Inc
Category: otc | Type: HUMAN OTC DRUG LABEL
Date: 20241212

ACTIVE INGREDIENTS: OCTINOXATE 71 mg/1 mL; OCTOCRYLENE 38 mg/1 mL; OCTISALATE 45 mg/1 mL; OXYBENZONE 28 mg/1 mL; AVOBENZONE 25 mg/1 mL
INACTIVE INGREDIENTS: WATER; BUTYLENE GLYCOL; ALKYL (C12-15) BENZOATE; GLYCERIN; GLYCERYL MONOSTEARATE; PEG-100 STEARATE; MICA; CETEARYL OLIVATE; CYCLOMETHICONE 5; SORBITAN OLIVATE; STEARIC ACID; CETOSTEARYL ALCOHOL; DIMETHICONE; .ALPHA.-TOCOPHEROL ACETATE, D-; COCONUT OIL; SHEA BUTTER; PHENOXYETHANOL; CAPRYLYL GLYCOL; TROMETHAMINE; EDETATE DISODIUM ANHYDROUS; LEVOMENOL; SILICON DIOXIDE; STANNIC OXIDE

Glow Radiant Moisturizer SPF 15

Active Ingredients

Octinoxate 7.1%

Octocrylene 3.8%

Octisalate 4.5%

Oxybenzone 2.8%

Avobenzone 2.5%

Purpose

Sunscreen

Uses

- Helps prevent sunburn.
- If used as directed with other sun protection measures (see), decreases the risk of skin cancer and early skin agining caused by the sun Direction

Warnings

For external use only.

Do not use

on damaged or broken skin.

When using this product

keep out of eyes. Rinse with water to remove.

Stop use and ask a doctor

if rash occurs.

Keep out of reach of children.

If product is swallowed, get medical help or contact a Poison Control Center right away.

Directions

• apply liberally 15 minutes before sun exposure. • reapply at least every 2 hours. • use a water resistant sunscreen if swimming or sweating. • Spending time in the sun increases your risk of sun cancer and early skin aging. To decrease this risk, regularly use a sunscreen with a Broad Spectrum SPF value of 15 or higher and other sun protection measures including: For sunscreen use: Sun Protection Measures:

• limit time in the sun, especially from 10 a.m.-2 p.m.

• wear long-sleeved shirts, pants, hats and sunglasses

• children under 6 months of age: Ask a doctor.

Inactive Ingredients

Water (Aqua), Butylene Glycol, C12-15 Alkyl Benzoate, Glycerin, Glyceryl Stearate, PEG-100 Stearate, Mica, Cetearyl Olivate, Cyclopentasiloxane, Sorbitan Olivate, Stearic Acid, Cetearyl Alcohol, Dimethicone, Tocopheryl Acetate (Ve), Cocos Nucifera (Coconut) Oil, Butyrospermum Parkii (Shea Butter), Hydrolyzed Hyaluronic Acid, Phenoxyethanol, Caprylyl Glycol, Acrylates/Polytrimethylsiloxymethacrylate Copolymer, Acrylates/C10-30 Alkyl Acrylate Crosspolymer, Tromethamine, Fragrance (Parfum), Disodium EDTA, Bisabolol, Synthetic Fluorphlogopite, Silica, Tin Oxide, MAY CONTAIN: Titanium Dioxide (CI 77891), Red 40 (CI 16035), Yellow 5 (CI 19140)

Questions or comments?

1-855-353-7320